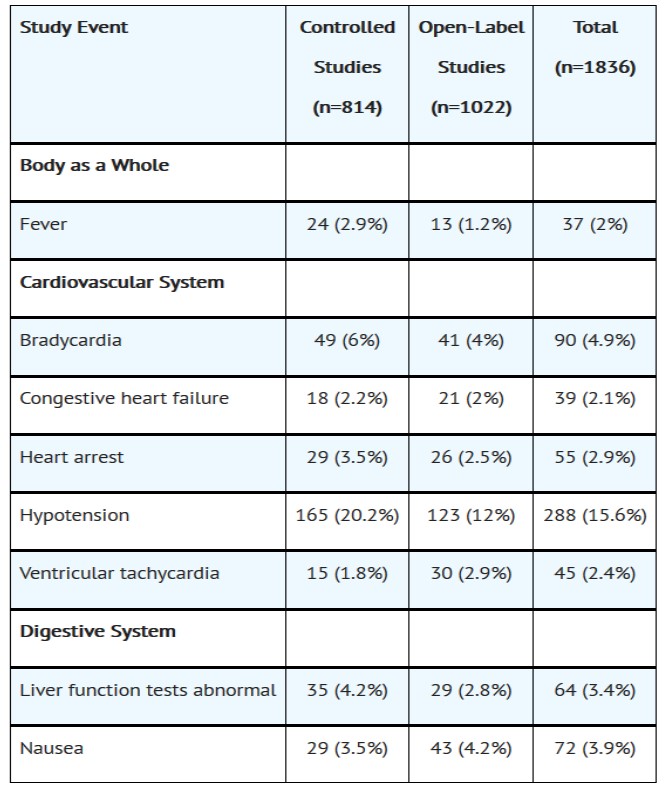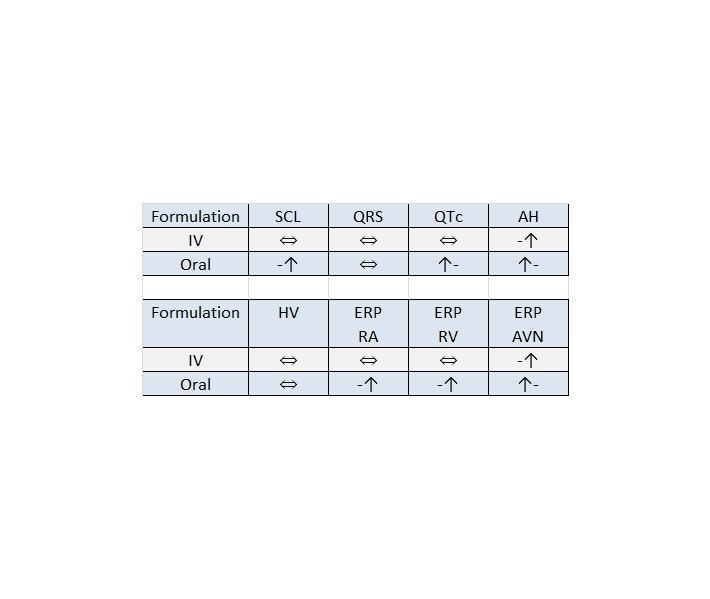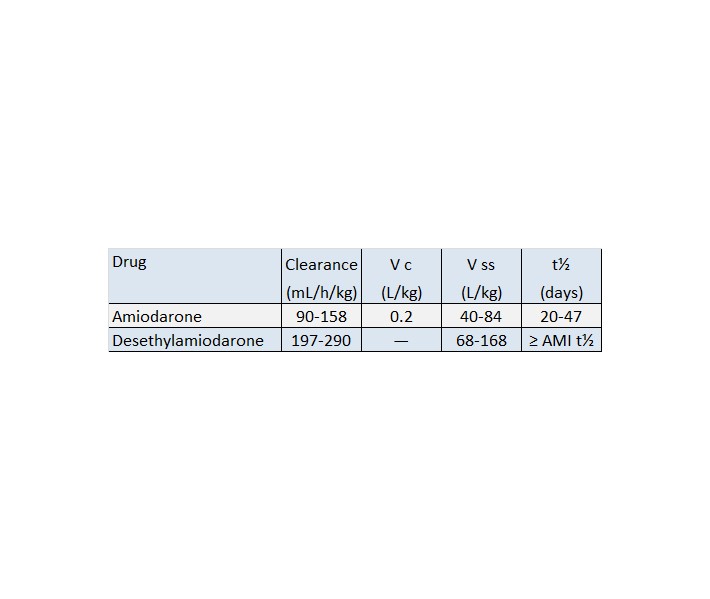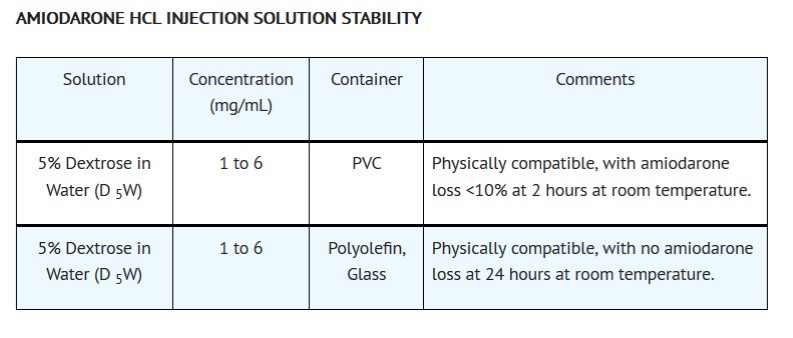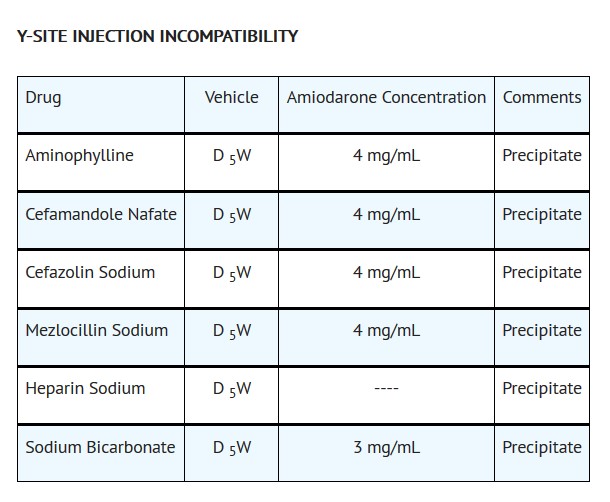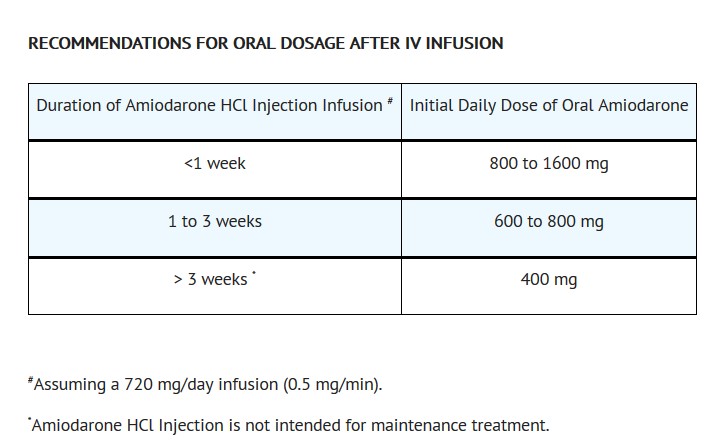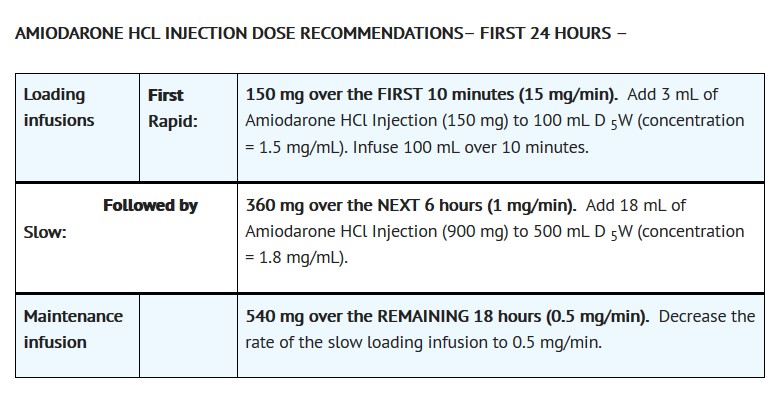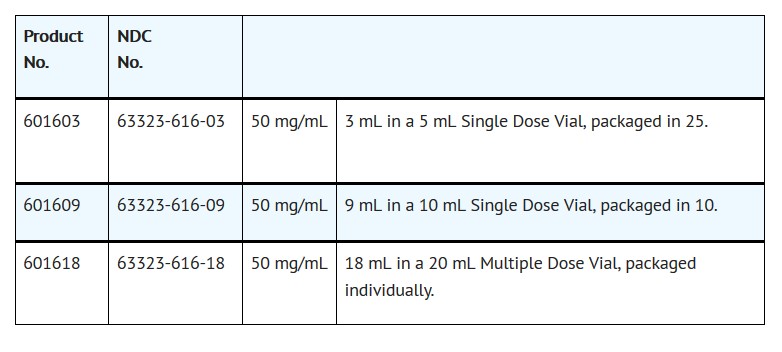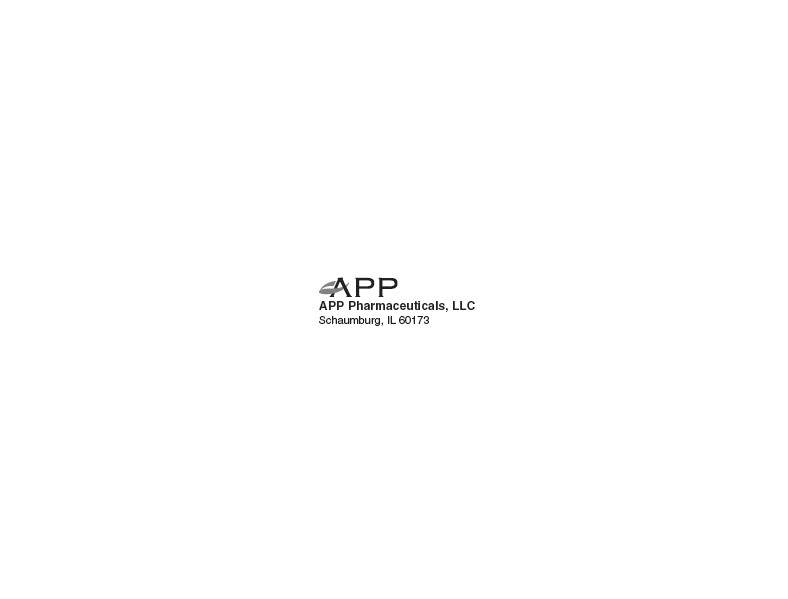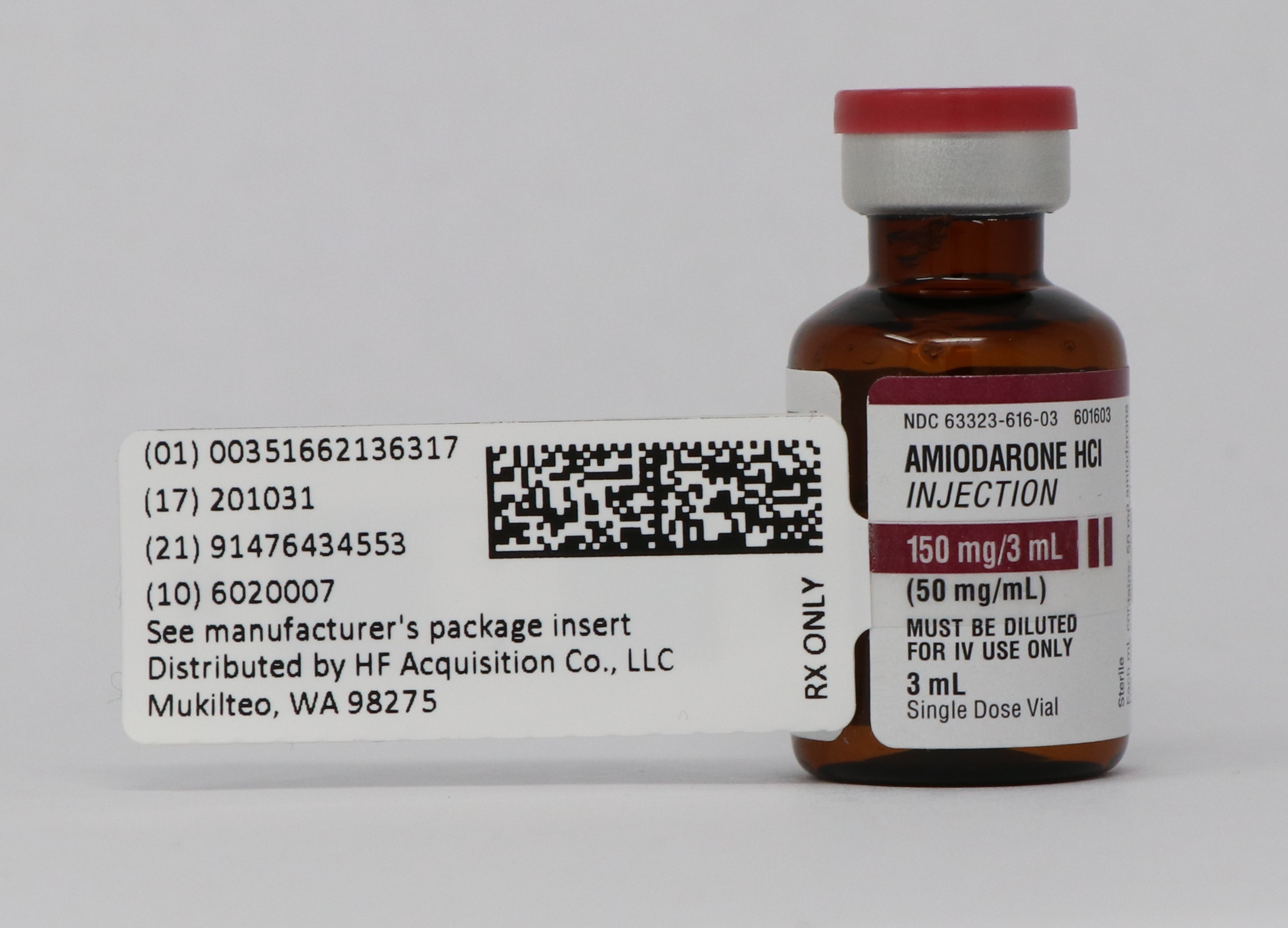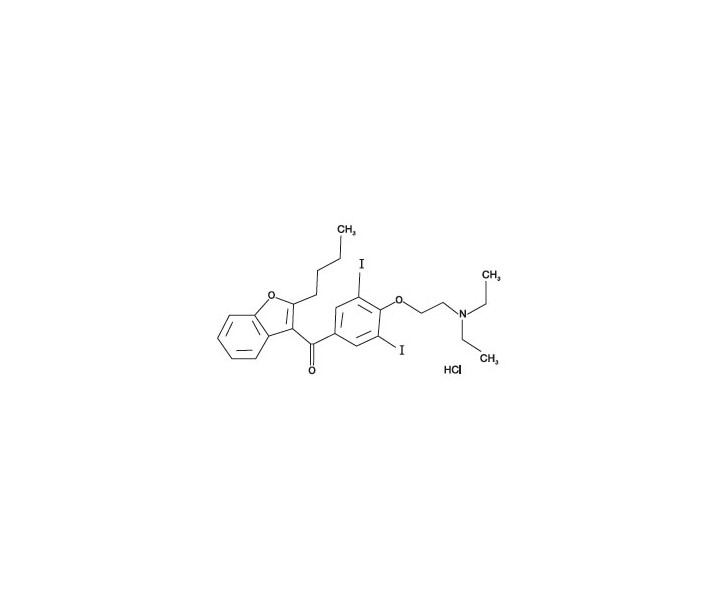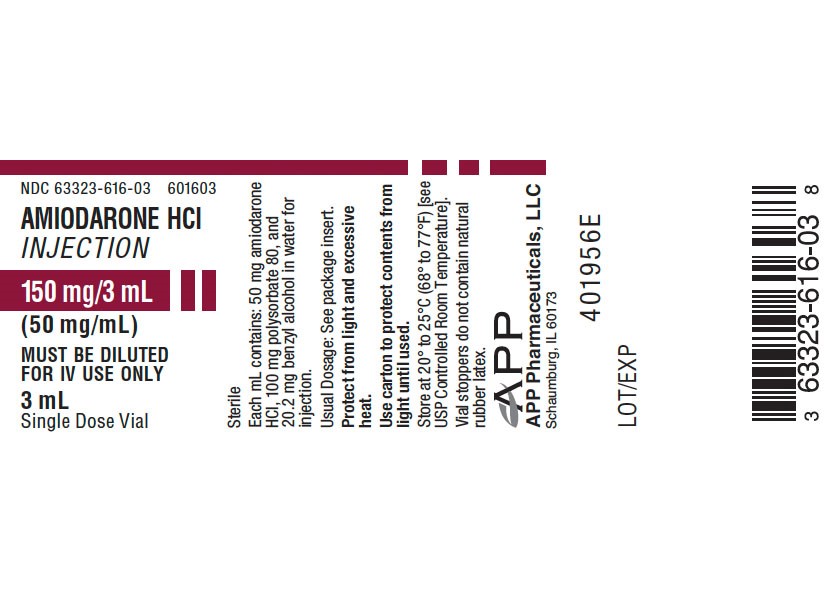 DRUG LABEL: AMIODARONE HCI
NDC: 51662-1363 | Form: INJECTION, SOLUTION
Manufacturer: HF Acquisition Co LLC, DBA HealthFirst
Category: prescription | Type: HUMAN PRESCRIPTION DRUG LABEL
Date: 20221210

ACTIVE INGREDIENTS: AMIODARONE HYDROCHLORIDE 50 mg/1 mL
INACTIVE INGREDIENTS: BENZYL ALCOHOL 20.2 mg/1 mL; POLYSORBATE 80 100 mg/1 mL

AMIODARONE HCI INJECTION 150 mg/3 mL (50 mg/mL) 3 mL VIAL

SPL UNCLASSIFIED

Rx only

This product’s label may have been revised after this insert was used in production. For further product information and current package insert, please visit www.APPpharma.com or call our medical information and safety department toll-free at 1-800-551-717

DESCRIPTION

Amiodarone Hydrochloride Injection, for intravenous use, contains amiodarone HCl, a class III antiarrhythmic drug. Amiodarone HCl is (2-butyl-3-benzofuranyl)[4-[2-(diethylamino)ethoxy]-3,5-diiodophenyl] methanone hydrochloride. Amiodarone HCl has the following structural formula:

C 25H 29I 2NO 3•HCl M.W. 681.78

Amiodarone HCl is a white to slightly yellow crystalline powder, and is very slightly soluble in water. It contains 37.3% iodine by weight. Amiodarone HCl Injection is a sterile clear, pale-yellow micellular solution visually free from particulates. Each mL of the Amiodarone HCl Injection formulation contains 50 mg of amiodarone HCl, 20.2 mg of benzyl alcohol, 100 mg of polysorbate 80, and water for injection.

Amiodarone HCl injection contains polysorbate 80, which is known to leach di-(2-ethylhexyl)phthalate (DEHP) from polyvinylchloride (PVC) (see DOSAGE & ADMINISTRATION).

CLINICAL PHARMACOLOGY

Mechanisms of Action

Amiodarone is generally considered a class III antiarrhythmic drug, but it possesses electrophysiologic characteristics of all four Vaughan Williams classes. Like class I drugs, amiodarone blocks sodium channels at rapid pacing frequencies, and like class II drugs, it exerts a noncompetitive antisympathetic action. One of its main effects, with prolonged administration, is to lengthen the cardiac action potential, a class III effect. The negative chronotropic effect of amiodarone in nodal tissues is similar to the effect of class IV drugs. In addition to blocking sodium channels, amiodarone blocks myocardial potassium channels, which contributes to slowing of conduction and prolongation of refractoriness. The antisympathetic action and the block of calcium and potassium channels are responsible for the negative dromotropic effects on the sinus node and for the slowing of conduction and prolongation of refractoriness in the atrioventricular (AV) node. Its vasodilatory action can decrease cardiac workload and consequently myocardial oxygen consumption.

Amiodarone HCl Injection administration prolongs intranodal conduction (Atrial-His, AH) and refractoriness of the atrioventricular node (ERP AVN), but has little or no effect on sinus cycle length (SCL), refractoriness of the right atrium and right ventricle (ERP RA and ERP RV), repolarization (QTc), intraventricular conduction (QRS), and infranodal conduction (His-ventricular, HV). A comparison of the electrophysiologic effects of amiodarone HCl injection and oral amiodarone is shown in the table below.

EFFECTS OF INTRAVENOUS AND

ORAL AMIODARONE ON

ELECTROPHYSIOLOGIC PARAMETERS

⇔No change

At higher doses (>10 mg/kg) of amiodarone HCl injection, prolongation of the ERP RV and modest prolongation of the QRS have been seen. These differences between oral and IV administration suggest that the initial acute effects of amiodarone HCl injection may be predominantly focused on the AV node, causing an intranodal conduction delay and increased nodal refractoriness due to slow channel blockade (class IV activity) and noncompetitive adrenergic antagonism (class II activity).

Pharmacokinetics and Metabolism

Amiodarone exhibits complex disposition characteristics after intravenous administration. Peak serum concentrations after single 5 mg/kg 15-minute intravenous infusions in healthy subjects range between 5 and 41 mg/L. Peak concentrations after 10-minute infusions of 150 mg amiodarone HCl injection in patients with ventricular fibrillation (VF) or hemodynamically unstable ventricular tachycardia (VT) range between 7 and 26 mg/L. Due to rapid distribution, serum concentrations decline to 10% of peak values within 30 to 45 minutes after the end of the infusion. In clinical trials, after 48 hours of continued infusions (125, 500 or 1000 mg/day) plus supplemental (150 mg) infusions (for recurrent arrhythmias), amiodarone mean serum concentrations between 0.7 to 1.4 mg/L were observed (n=260).

N-desethylamiodarone (DEA) is the major active metabolite of amiodarone in humans. DEA serum concentrations above 0.05 mg/L are not usually seen until after several days of continuous infusion but with prolonged therapy reach approximately the same concentration as amiodarone. Amiodarone is metabolized to desethylamiodarone by the cytochrome P450 (CYP450) enzyme group, specifically cytochrome P450 3A4 (CYP3A4) and CYP2C8. The CYP3A4 isoenzyme is present in both the liver and intestines. The highly variable systemic availability of oral amiodarone may be attributed potentially to large interindividual variability in CYP3A4 activity.

Amiodarone is eliminated primarily by hepatic metabolism and biliary excretion and there is negligible excretion of amiodarone or DEA in urine. Neither amiodarone nor DEA is dialyzable. Amiodarone and DEA cross the placenta and both appear in breast milk.

No data are available on the activity of DEA in humans, but in animals, it has significant electrophysiologic and antiarrhythmic effects generally similar to amiodarone itself. DEA’s precise role and contribution to the antiarrhythmic activity of oral amiodarone are not certain. The development of maximal ventricular class III effects after oral amiodarone administration in humans correlates more closely with DEA accumulation over time than with amiodarone accumulation. On the other hand (see Clinical Trials), after amiodarone HCl injection administration, there is evidence of activity well before significant concentrations of DEA are attained.

The following table summarizes the mean ranges of pharmacokinetic parameters of amiodarone reported in single dose IV (5 mg/kg over 15 min) studies of healthy subjects.

PHARMACOKINETIC PROFILE AFTER

AMIODARONE HCl INJECTION ADMINISTRATION

Notes: V c and V ss denote the central and steady-state volumes of distribution from IV studies.

“—” denotes not available.

Desethylamiodarone clearance and volume involve an unknown biotransformation factor.

The systemic availability of oral amiodarone in healthy subjects ranges between 33% and 65%. From in vitro studies, the protein binding of amiodarone is >96%.

In clinical studies of 2 to 7 days, clearance of amiodarone after intravenous administration in patients with VT and VF ranged between 220 and 440 mL/h/kg. Age, sex, renal disease, and hepatic disease (cirrhosis) do not have marked effects on the disposition of amiodarone or DEA. Renal impairment does not influence the pharmacokinetics of amiodarone. After a single dose of amiodarone HCl injection in cirrhotic patients, significantly lower C max and average concentration values are seen for DEA, but mean amiodarone levels are unchanged. Normal subjects over 65 years of age show lower clearances (about 100 mL/h/kg) than younger subjects (about 150 mL/h/kg) and an increase in t½ from about 20 to 47 days. In patients with severe left ventricular dysfunction, the pharmacokinetics of amiodarone are not significantly altered but the terminal disposition t½ of DEA is prolonged. Although no dosage adjustment for patients with renal, hepatic, or cardiac abnormalities has been defined during chronic treatment with oral amiodarone, close clinical monitoring is prudent for elderly patients and those with severe left ventricular dysfunction.

There is no established relationship between drug concentration and therapeutic response for short-term intravenous use. Steady-state amiodarone concentrations of 1 to 2.5 mg/L have been associated with antiarrhythmic effects and acceptable toxicity following chronic oral amiodarone therapy.

Pharmacodynamics

Amiodarone HCl injection has been reported to produce negative inotropic and vasodilatory effects in animals and humans. In clinical studies of patients with refractory VF or hemodynamically unstable VT, treatment-emergent, drug related hypotension occurred in 288 of 1836 patients (16%) treated with amiodarone HCl injection. No correlations were seen between the baseline ejection fraction and the occurrence of clinically significant hypotension during infusion of amiodarone HCl injection.

Clinical Trials

Apart from studies in patients with VT or VF, described below, there are two other studies of amiodarone showing an antiarrhythmic effect before significant levels of DEA could have accumulated. A placebo-controlled study of IV amiodarone (300 mg over 2 hours followed by 1200 mg/day) in post-coronary artery bypass graft patients with supraventricular and 2- to 3-consecutive-beat ventricular arrhythmias showed a reduction in arrhythmias from 12 hours on. A baseline-controlled study using a similar IV regimen in patients with recurrent, refractory VT/VF also showed rapid onset of antiarrhythmic activity; amiodarone therapy reduced episodes of VT by 85% compared to baseline.

The acute effectiveness of amiodarone HCl injection in suppressing recurrent VF or hemodynamically unstable VT is supported by two randomized, parallel, dose-response studies of approximately 300 patients each. In these studies, patients with at least two episodes of VF or hemodynamically unstable VT in the preceding 24 hours were randomly assigned to receive doses of approximately 125 or 1000 mg over the first 24 hours, an 8-fold difference. In one study, a middle dose of approximately 500 mg was evaluated. The dose regimen consisted of an initial rapid loading infusion, followed by a slower 6-hour loading infusion, and then an 18-hour maintenance infusion. The maintenance infusion was continued up to hour 48. Additional 10-minute infusions of 150 mg amiodarone HCl injection were given for “breakthrough” VT/VF more frequently to the 125 mg dose group, thereby considerably reducing the planned 8-fold differences in total dose to 1.8- and 2.6-fold, respectively, in the two studies.

The prospectively defined primary efficacy end point was the rate of VT/VF episodes per hour. For both studies, the median rate was 0.02 episodes per hour in patients receiving the high dose and 0.07 episodes per hour in patients receiving the low dose, or approximately 0.5 versus 1.7 episodes per day (p=0.07, 2-sided, in both studies). In one study, the time to first episode of VT/VF was significantly prolonged (approximately 10 hours in patients receiving the low dose and 14 hours in patients receiving the high dose). In both studies, significantly fewer supplemental infusions were given to patients in the high-dose group. Mortality was not affected in these studies; at the end of double-blind therapy or after 48 hours, all patients were given open access to whatever treatment (including amiodarone HCl injection) was deemed necessary.

INDICATIONS & USAGE

Amiodarone HCl injection is indicated for initiation of treatment and prophylaxis of frequently recurring ventricular fibrillation and hemodynamically unstable ventricular tachycardia in patients refractory to other therapy. Amiodarone HCl injection also can be used to treat patients with VT/VF for whom oral amiodarone is indicated, but who are unable to take oral medication. During or after treatment with amiodarone HCl injection, patients may be transferred to oral amiodarone therapy (see DOSAGE & ADMINISTRATION).

Amiodarone HCl injection should be used for acute treatment until the patient’s ventricular arrhythmias are stabilized. Most patients will require this therapy for 48 to 96 hours, but amiodarone HCl injection may be safely administered for longer periods if necessary.

CONTRAINDICATIONS

Amiodarone HCl injection is contraindicated in patients with known hypersensitivity to any of the components of amiodarone HCl injection, including iodine, or in patients with cardiogenic shock, marked sinus bradycardia, and second- or third-degree AV block unless a functioning pacemaker is available.

WARNINGS

Hypotension

Hypotension is the most common adverse effect seen with Amiodarone HCl injection. In clinical trials, treatment-emergent, drug-related hypotension was reported as an adverse effect in 288 (16%) of 1836 patients treated with amiodarone HCl injection. Clinically significant hypotension during infusions was seen most often in the first several hours of treatment and was not dose-related, but appeared to be related to the rate of infusion. Hypotension necessitating alterations in amiodarone HCl injection therapy was reported in 3% of patients, with permanent discontinuation required in less than 2% of patients.

Hypotension should be treated initially by slowing the infusion; additional standard therapy may be needed, including the following: vasopressor drugs, positive inotropic agents, and volume expansion. The initial rate of infusion should be monitored closely and should not exceed that prescribed in DOSAGE & ADMINISTRATION.

In some cases, hypotension may be refractory resulting in fatal outcome (see ADVERSE REACTIONS, Post-marketing Reports).

Bradycardia and AV Stock

Drug-related bradycardia occurred in 90 (4.9%) of 1836 patients in clinical trials while they were receiving amiodarone HCl injection for life-threatening VT/VF; it was not dose-related. Bradycardia should be treated by slowing the infusion rate or discontinuing amiodarone HCl injection. In some patients, inserting a pacemaker is required. Despite such measures, bradycardia was progressive and terminal in 1 patient during the controlled trials. Patients with a known predisposition to bradycardia or AV block should be treated with amiodarone HCl injection in a setting where a temporary pacemaker is available.

Liver Enzyme Elevations

Elevations of blood hepatic enzyme values – alanine aminotransferase (ALT), aspartate aminotransferase (AST), and gamma-glutamyl transferase (GGT) – are seen commonly in patients with immediately life-threatening VT/VF. Interpreting elevated AST activity can be difficult because the values may be elevated in patients who have had recent myocardial infarction, congestive heart failure, or multiple electrical defibrillations. Approximately 54% of patients receiving amiodarone HCl injection in clinical studies had baseline liver enzyme elevations, and 13% had clinically significant elevations. In 81% of patients with both baseline and on-therapy data available, the liver enzyme elevations either improved during therapy or remained at baseline levels. Baseline abnormalities in hepatic enzymes are not a contraindication to treatment.

Acute, centrolobular confluent hepatocellular necrosis leading to hepatic coma, acute renal failure, and death has been associated with the administration of amiodarone HCl injection at a much higher loading dose concentration and much faster rate of infusion than recommended in DOSAGE & ADMINISTRATION. Therefore, the initial concentration and rate of infusion should be monitored closely and should not exceed that prescribed in DOSAGE & ADMINISTRATION (see DOSAGE & ADMINISTRATION).

In patients with life-threatening arrhythmias, the potential risk of hepatic injury should be weighed against the potential benefit of amiodarone HCl injection therapy, but patients receiving amiodarone HCl injection should be monitored carefully for evidence of progressive hepatic injury. Consideration should be given to reducing the rate of administration or withdrawing amiodarone HCl injection in such cases.

Proarrhythmia

Like all antiarrhythmic agents, amiodarone HCl injection may cause a worsening of existing arrhythmias or precipitate a new arrhythmia. Proarrhythmia, primarily torsade de pointes (TdP), has been associated with prolongation by amiodarone HCl injection of the QTc interval to 500 ms or greater. Although QTc prolongation occurred frequently in patients receiving amiodarone HCl injection, torsade de pointes or new-onset VF occurred infrequently (less than 2%). Patients should be monitored for QTc prolongation during infusion with amiodarone HCl injection. Combination of amiodarone with other antiarrhythmic therapy that prolongs the QTc should be reserved for patients with life-threatening ventricular arrhythmias who are incompletely responsive to a single agent.

Fluoroquinolones, macrolide antibiotics, and azoles are known to cause QTc prolongation. There have been reports of QTc prolongation, with or without TdP, in patients taking amiodarone when fluoroquinolones, macrolide antibiotics, or azoles were administered concomitantly (see Drug Interactions, Other reported interactions with amiodarone).

The need to coadminister amiodarone with any other drug known to prolong the QTc interval must be based on a careful assessment of the potential risks and benefits of doing so for each patient.

A careful assessment of the potential risks and benefits of administering amiodarone HCl injection must be made in patients with thyroid dysfunction due to the possibility of arrhythmia breakthrough or exacerbation of arrhythmia, which may result in death, in these patients.

Pulmonary Disorders

Early-onset Pulmonary Toxicity

There have been postmarketing reports of acute-onset (days to weeks) pulmonary injury in patients treated with intravenous amiodarone. Findings have included pulmonary infiltrates and/or mass on X-ray, bronchospasm, wheezing, fever, dyspnea, cough, hemoptysis, and hypoxia. Some cases have progressed to respiratory failure and/or death.

ARDS

Two percent (2%) of patients were reported to have adult respiratory distress syndrome (ARDS) during clinical studies involving 48 hours of therapy. ARDS is a disorder characterized by bilateral, diffuse pulmonary infiltrates with pulmonary edema and varying degrees of respiratory insufficiency. The clinical and radiographic picture can arise after a variety of lung injuries, such as those resulting from trauma, shock, prolonged cardiopulmonary resuscitation, and aspiration pneumonia, conditions present in many of the patients enrolled in the clinical studies. There have been postmarketing reports of ARDS in intravenous amiodarone patients. Intravenous amiodarone may play a role in causing or exacerbating pulmonary disorders in those patients.

Postoperatively, occurrences of ARDS have been reported in patients receiving oral amiodarone therapy who have undergone either cardiac or noncardiac surgery. Although patients usually respond well to vigorous respiratory therapy, in rare instances the outcome has been fatal. Until further studies have been performed, it is recommended that FiO 2 and the determinants of oxygen delivery to the tissues (e.g., SaO 2, PaO 2) be closely monitored in patients on amiodarone.

Pulmonary Fibrosis

Only 1 of more than 1000 patients treated with amiodarone HCl injection in clinical studies developed pulmonary fibrosis. In that patient, the condition was diagnosed 3 months after treatment with amiodarone HCl injection, during which time she received oral amiodarone. Pulmonary toxicity is a well-recognized complication of long-term amiodarone use (see labeling for oral amiodarone).

Loss of Vision

Cases of optic neuropathy and/or optic neuritis, usually resulting in visual impairment, have been reported in patients treated with oral amiodarone. In some cases, visual impairment has progressed to permanent blindness. Amiodarone HCl injection is indicated for initiation of treatment and prophylaxis of frequently recurring ventricular fibrillation (VF) and hemodynamically unstable ventricular tachycardia (VT) in patients refractory to other therapy and can also be used to treat patients with VT/VF for whom oral amiodarone is indicated, but who are unable to take oral medication. Optic neuropathy and/or neuritis may occur at any time following initiation of therapy. A causal relationship to the drug has not been clearly established. If symptoms of visual impairment appear, such as changes in visual acuity and decreases in peripheral vision, prompt ophthalmic examination is recommended. Appearance of optic neuropathy and/or neuritis calls for re-evaluation of amiodarone therapy. The risks and complications of antiarrhythmic therapy with amiodarone must be weighed against its benefits in patients whose lives are threatened by cardiac arrhythmias. Regular ophthalmic examination, including fundoscopy and slit-lamp examination, is recommended during administrations of amiodarone (see ADVERSE REACTIONS).

Long-Term Use

See labeling for oral amiodarone. There has been limited experience in patients receiving amiodarone HCl injection for longer than 3 weeks.

Thyrotoxicosis

Amiodarone-induced hyperthyroidism may result in thyrotoxicosis and/or the possibility of arrhythmia breakthrough or aggravation. There have been reports of death associated with amiodarone-induced thyrotoxicosis. IF ANY NEW SIGNS OF ARRHYTHMIA APPEAR, THE POSSIBILITY OF HYPERTHYROIDISM SHOULD BE CONSIDERED (see PRECAUTIONS, Thyroid Abnormalities).

Neonatal Hypo- or Hyperthyroidism

Although amiodarone use during pregnancy is uncommon, there have been a small number of published reports of congenital goiter/hypothyroidism and hyperthyroidism associated with its oral administration. If amiodarone HCl injection is administered during pregnancy, the patient should be apprised of the potential hazard to the fetus.

PRECAUTIONS

Amiodarone HCl injection should be administered only by physicians who are experienced in the treatment of life-threatening arrhythmias, who are thoroughly familiar with the risks and benefits of amiodarone therapy, and who have access to facilities adequate for monitoring the effectiveness and side effects of treatment.

Thyroid Abnormalities

Amiodarone inhibits peripheral conversion of thyroxine (T 4) to triiodothyronine (T 3) and may cause increased thyroxine levels, decreased T 3 levels, and increased levels of inactive reverse T 3 (rT 3) in clinically euthyroid patients. It is also a potential source of large amounts of inorganic iodine. Because of its release of inorganic iodine, or perhaps for other reasons, amiodarone can cause either hypothyroidism or hyperthyroidism. Thyroid function should be monitored prior to treatment and periodically thereafter, particularly in elderly patients, and in any patient with a history of thyroid nodules, goiter, or other thyroid dysfunction. Because of the slow elimination of amiodarone and its metabolites, high plasma iodide levels, altered thyroid function, and abnormal thyroid-function tests may persist for several weeks or even months following amiodarone withdrawal.

Hypothyroidism has been reported in 2 to 4% of patients in most series, but in 8 to 10% in some series. This condition may be identified by relevant clinical symptoms and particularly by elevated serum TSH levels. In some clinically hypothyroid amiodarone-treated patients, free thyroxine index values may be normal. Hypothyroidism is best managed by amiodarone dose reduction and/or thyroid hormone supplement. However, therapy must be individualized, and it may be necessary to discontinue amiodarone tablets in some patients.

Hyperthyroidism occurs in about 2% of patients receiving amiodarone, but the incidence may be higher among patients with prior inadequate dietary iodine intake. Amiodarone-induced hyperthyroidism usually poses a greater hazard to the patient than hypothyroidism because of the possibility of thyrotoxicosis and/or arrhythmia breakthrough or aggravation, all of which may result in death. There have been reports of death associated with amiodarone-induced thyrotoxicosis. IF ANY NEW SIGNS OF ARRHYTHMIA APPEAR, THE POSSIBILITY OF HYPERTHYROIDISM SHOULD BE CONSIDERED.

Hyperthyroidism is best identified by relevant clinical symptoms and signs, accompanied usually by abnormally elevated levels of serum T 3 RIA, and further elevations of serum T 4, and a subnormal serum TSH level (using a sufficiently sensitive TSH assay). The finding of a flat TSH response to TRH is confirmatory of hyperthyroidism and may be sought in equivocal cases. Since arrhythmia breakthroughs may accompany amiodarone-induced hyperthyroidism, aggressive medical treatment is indicated, including, if possible, dose reduction or withdrawal of amiodarone.

The institution of antithyroid drugs, β-adrenergic blockers and/or temporary corticosteroid therapy may be necessary. The action of antithyroid drugs may be especially delayed in amiodarone-induced thyrotoxicosis because of substantial quantities of preformed thyroid hormones stored in the gland. There have been reports of death associated with amiodarone-induced thyrotoxicosis. Radioactive iodine therapy is contraindicated because of the low radioiodine uptake associated with amiodarone-induced hyperthyroidism. Amiodarone-induced hyperthyroidism may be followed by a transient period of hypothyroidism (see WARNINGS, Thyrotoxicosis).

When aggressive treatment of amiodarone-induced thyrotoxicosis has failed or amiodarone cannot be discontinued because it is the only drug effective against the resistant arrhythmia, surgical management may be an option. Experience with thyroidectomy as a treatment for amiodarone-induced thyrotoxicosis is limited, and this form of therapy could induce thyroid storm. Therefore, surgical and anesthetic management require careful planning.

There have been postmarketing reports of thyroid nodules/thyroid cancer in patients treated with amiodarone. In some instances hyperthyroidism was also present (see WARNINGS and ADVERSE REACTIONS).

Surgery

Close perioperative monitoring is recommended in patients undergoing general anesthesia who are on amiodarone therapy as they may be more sensitive to the myocardial depressant and conduction defects of halogenated inhalational anesthetics.

Corneal Refractive Laser Surgery

Patients should be advised that most manufacturers of corneal refractive laser surgery devices contraindicate that procedure in patients taking amiodarone.

Drug Interactions

Amiodarone is metabolized to desethylamiodarone by the cytochrome P450 (CYP450) enzyme group, specifically cytochrome P450 3A4 (CYP3A4) and CYP2C8. The CYP3A4 isoenzyme is present in both the liver and intestines (see CLINICAL PHARMACOLOGY, Pharmacokinetics and Metabolism). Amiodarone is an inhibitor of CYP3A4 and p-glycoprotein. Therefore, amiodarone has the potential for interactions with drugs or substances that may be substrates, inhibitors or inducers of CYP3A4 and substrates of p-glycoprotein. While only a limited number of in vivo drug-drug interactions with amiodarone have been reported, chiefly with the oral formulation, the potential for other interactions should be anticipated. This is especially important for drugs associated with serious toxicity, such as other antiarrhythmics. If such drugs are needed, their dose should be reassessed and, where appropriate, plasma concentration measured. In view of the long and variable half-life of amiodarone, potential for drug interactions exists not only with concomitant medication but also with drugs administered after discontinuation of amiodarone.

Since amiodarone is a substrate for CYP3A4 and CYP2C8, drugs/substances that inhibit these isoenzymes may decrease the metabolism and increase serum concentration of amiodarone. Reported examples include the following:

Protease Inhibitors:

Protease inhibitors are known to inhibit CYP3A4 to varying degrees. A case report of one patient taking amiodarone 200 mg and indinavir 800 mg three times a day resulted in increases in amiodarone concentrations from 0.9 mg/L to 1.3 mg/L. DEA concentrations were not affected. There was no evidence of toxicity. Monitoring for amiodarone toxicity and serial measurement of amiodarone serum concentration during concomitant protease inhibitor therapy should be considered.

Histamine H 1 antagonists:

Loratadine, a non-sedating antihistaminic, is metabolized primarily by CYP3A4. QT interval prolongation and torsade de pointes have been reported with the co-administration of loratadine and amiodarone.

Histamine H 2 antagonists:

Cimetidine inhibits CYP3A4 and can increase serum amiodarone levels.

Antidepressants:

Trazodone, an antidepressant, is metabolized primarily by CYP3A4. QT interval prolongation and torsade de pointes have been reported with the co-administration of trazodone and amiodarone.

Other substances:

Grapefruit juice given to healthy volunteers increased amiodarone AUC by 50% and C max by 84%, resulting in increased plasma levels of amiodarone. Grapefruit juice should not be taken during treatment with oral amiodarone. This information should be considered when changing from intravenous amiodarone to oral amiodarone (see DOSAGE & ADMINISTRATION, Intravenous to Oral Transition).

Amiodarone inhibits p-glycoprotein and certain CYP450 enzymes, including CYP1A2, CYP2C9, CYP2D6, and CYP3A4. This inhibition can result in unexpectedly high plasma levels of other drugs which are metabolized by those CYP450 enzymes or are substrates of p-glycoprotein. Reported examples of this interaction include the following:

Immunosuppressives:

Cyclosporine (CYP3A4 substrate) administered in combination with oral amiodarone has been reported to produce persistently elevated plasma concentrations of cyclosporine resulting in elevated creatinine, despite reduction in dose of cyclosporine.

HMG-CoA Reductase Inhibitors:

Simvastatin (CYP3A4 substrate) in combination with amiodarone has been associated with reports of myopathy/rhabdomyolysis.

Cardiovasculars:

Cardiac glycosides: In patients receiving digoxin therapy, administration of oral amiodarone regularly results in an increase in serum digoxin concentration that may reach toxic levels with resultant clinical toxicity. Amiodarone taken concomitantly with digoxin increases the serum digoxin concentration by 70% after one day. On administration of oral amiodarone, the need for digitalis therapy should be reviewed and the dose reduced by approximately 50% or discontinued. If digitalis treatment is continued, serum levels should be closely monitored and patients observed for clinical evidence of toxicity. These precautions probably should apply to digitoxin administration as well.

Antiarrhythmics: Other antiarrhythmic drugs, such as quinidine, procainamide, disopyramide, and phenytoin, have been used concurrently with amiodarone. There have been case reports of increased steady-state levels of quinidine, procainamide, and phenytoin during concomitant therapy with amiodarone. Phenytoin decreases serum amiodarone levels. Amiodarone taken concomitantly with quinidine increases quinidine serum concentration by 33% after two days. Amiodarone taken concomitantly with procainamide for less than seven days increases plasma concentrations of procainamide and n-acetyl procainamide by 55% and 33%, respectively. Quinidine and procainamide doses should be reduced by one-third when either is administered with amiodarone. Plasma levels of flecainide have been reported to increase in the presence of oral amiodarone; because of this, the dosage of flecainide should be adjusted when these drugs are administered concomitantly. In general, any added antiarrhythmic drug should be initiated at a lower than usual dose with careful monitoring. Combination of amiodarone with other antiarrhythmic therapy should be reserved for patients with life-threatening ventricular arrhythmias who are incompletely responsive to a single agent or incompletely responsive to amiodarone. During transfer to oral amiodarone, the dose levels of previously administered agents should be reduced by 30 to 50% several days after the addition of oral amiodarone (see DOSAGE & ADMINISTRATION, Intravenous to Oral Transition). The continued need for the other antiarrhythmic agent should be reviewed after the effects of amiodarone have been established, and discontinuation ordinarily should be attempted. If the treatment is continued, these patients should be particularly carefully monitored for adverse effects, especially conduction disturbances and exacerbation of tachyarrhythmias, as amiodarone is continued. In amiodarone-treated patients who require additional antiarrhythmic therapy, the initial dose of such agents should be approximately half of the usual recommended dose.

Antihypertensives: Amiodarone should be used with caution in patients receiving ß- receptor blocking agents (e.g., propranolol, a CYP3A4 inhibitor) or calcium channel antagonists (e.g., verapamil, a CYP3A4 substrate, and diltiazem, a CYP3A4 inhibitor) because of the possible potentiation of bradycardia, sinus arrest, and AV block; if necessary, amiodarone can continue to be used after insertion of a pacemaker in patients with severe bradycardia or sinus arrest.

Anticoagulants: Potentiation of warfarin-type (CYP2C9 and CYP3A4 substrate) anticoagulant response is almost always seen in patients receiving amiodarone and can result in serious or fatal bleeding. Since the concomitant administration of warfarin with amiodarone increases the prothrombin time by 100% after 3 to 4 days, the dose of the anticoagulant should be reduced by one-third to one-half, and prothrombin times should be monitored closely. A similar effect has been reported with fluindione, an oral vitamin K antagonist, when administered concomitantly with amiodarone.

Clopidogrel, an inactive thienopyridine prodrug, is metabolized in the liver by CYP3A4 to an active metabolite. A potential interaction between clopidogrel and amiodarone resulting in ineffective inhibition of platelet aggregation has been reported.

Some drugs/substances are known to accelerate the metabolism of amiodarone by stimulating the synthesis of CYP3A4 (enzyme induction). This may lead to low amiodarone serum levels and potential decrease in efficacy. Reported examples of this interaction include the following:

Antibiotics:

Rifampin is a potent inducer of CYP3A4. Administration of rifampin concomitantly with oral amiodarone has been shown to result in decreases in serum concentrations of amiodarone and desethylamiodarone.

Other substances, including herbal preparations:

St. John’s Wort (Hypericum perforatum) induces CYP3A4. Since amiodarone is a substrate for CYP3A4, there is the potential that the use of St. John’s Wort in patients receiving amiodarone could result in reduced amiodarone levels.

Other reported interactions with amiodarone:

Fentanyl: (CYP3A4 substrate) in combination with amiodarone may cause hypotension, bradycardia, and decreased cardiac output.

Sinus bradycardia has been reported with oral amiodarone in combination with lidocaine (CYP3A4 substrate) given for local anesthesia. Seizure, associated with increased lidocaine concentrations, has been reported with concomitant administration of intravenous amiodarone.

Dextromethorphan is a substrate for both CYP2D6 and CYP3A4. Amiodarone inhibits CYP2D6.

Cholestyramine increases enterohepatic elimination of amiodarone and may reduce its serum levels and t½.

Disopyramide increases QT prolongation which could cause arrhythmia.

Fluoroquinolones, macrolide antibiotics, and azoles are known to cause QTc prolongation. There have been reports of QTc prolongation, with or without TdP, in patients taking amiodarone when fluoroquinolones, macrolide antibiotics, or azoles were administered concomitantly (see PRECAUTIONS, Proarrhythmia).

Hemodynamic and electrophysiologic interactions have also been observed after concomitant administration with propranolol, diltiazem, and verapamil.

Volatile Anesthetic Agents:

(see PRECAUTIONS, Surgery).

In addition to the interactions noted above, chronic (> 2 weeks) oral amiodarone administration impairs metabolism of phenytoin, dextromethorphan, and methotrexate.

Electrolyte Disturbances

Patients with hypokalemia or hypomagnesemia should have the condition corrected whenever possible before being treated with amiodarone HCl injection, as these disorders can exaggerate the degree of QTc prolongation and increase the potential for TdP. Special attention should be given to electrolyte and acid-base balance in patients experiencing severe or prolonged diarrhea or in patients receiving concomitant diuretics.

Carcinogenesis, Mutagenesis, Impairment of Fertility

No carcinogenicity studies were conducted with amiodarone HCl injection. However, oral amiodarone caused a statistically significant, dose-related increase in the incidence of thyroid tumors (follicular adenoma and/or carcinoma) in rats. The incidence of thyroid tumors in rats was greater than the incidence in controls even at the lowest dose level tested, i.e., 5 mg/kg/day (approximately 0.08 times the maximum recommended human maintenance dose*).

Mutagenicity studies conducted with amiodarone HCl (Ames, micronucleus, and lysogenic induction tests) were negative.

No fertility studies were conducted with amiodarone HCl injection. However, in a study in which amiodarone HCl was orally administered to male and female rats, beginning 9 weeks prior to mating, reduced fertility was observed at a dose level of 90 mg/kg/day (approximately 1.4 times the maximum recommended human maintenance dose*).

*600 mg in a 50 kg patient (dose compared on a body surface area basis).

Pregnancy

Category D. See WARNINGS, Neonatal Hypo- or Hyperthyroidism.

In addition to causing infrequent congenital goiter/hypothyroidism and hyperthyroidism, amiodarone has caused a variety of adverse effects in animals.

In a reproductive study in which amiodarone was given intravenously to rabbits at dosages of 5,10, or 25 mg/kg per day (about 0.1, 0.3, and 0.7 times the maximum recommended human dose [MRHD] on a body surface area basis), maternal deaths occurred in all groups, including controls. Embryotoxicity (as manifested by fewer full-term fetuses and increased resorptions with concomitantly lower litter weights) occurred at dosages of 10 mg/kg and above. No evidence of embryotoxicity was observed at 5 mg/kg and no teratogenicity was observed at any dosages.

In a teratology study in which amiodarone was administered by continuous IV infusion to rats at dosages of 25, 50, or 100 mg/kg per day (about 0.4, 0.7, and 1.4 times the MRHD when compared on a body surface area basis), maternal toxicity (as evidenced by reduced weight gain and food consumption) and embryotoxicity (as evidenced by increased resorptions, decreased live litter size, reduced body weights, and retarded sternum and metacarpal ossification) were observed in the 100 mg/kg group.

Amiodarone HCl injection should be used during pregnancy only if the potential benefit to the mother justifies the risk to the fetus.

Nursing Mothers

Amiodarone and one of it’s major metabolites, desethylamiodarone (DEA), are excreted in human milk, suggesting that breast-feeding could expose the nursing infant to a significant dose of the drug. Nursing offspring of lactating rats administered amiodarone have demonstrated reduced viability and reduced body weight gains. The risk of exposing the infant to amiodarone should be weighed against the potential benefit of arrhythmia suppression in the mother. The mother should be advised to discontinue nursing.

Labor and Delivery

It is not known whether the use of amiodarone during labor or delivery has any immediate or delayed adverse effects. Preclinical studies in rodents have not shown any effect on the duration of gestation or on parturition.

Pediatric Use

The safety and efficacy of amiodarone in the pediatric population have not been established; therefore, its use in pediatric patients is not recommended. In a pediatric trial of 61 patients, aged 30 days to 15 years, hypotension (36%), bradycardia (20%), and atrio-ventricular block (15%) were common dose-related adverse events and were severe or life-threatening in some cases. Injection site reactions were seen in 5 (25%) of the 20 patients receiving intravenous amiodarone through a peripheral vein irrespective of dose regimen.

Amiodarone HCl injection contains the preservative benzyl alcohol (see DESCRIPTION). There have been reports of fatal “gasping syndrome” in neonates (children less than one month of age) following the administration of intravenous solutions containing the preservative benzyl alcohol. Symptoms include a striking onset of gasping respiration, hypotension, bradycardia, and cardiovascular collapse.

Geriatric Use

Clinical studies of amiodarone did not include sufficient numbers of subjects aged 65 and over to determine whether they respond differently from younger subjects. Other reported clinical experience has not identified differences in responses between the elderly and younger patients. In general, dose selection for an elderly patient should be cautious, usually starting at the low end of the dosing range, reflecting the greater frequency of decreased hepatic, renal, or cardiac function, and of concomitant disease or other drug therapy.

ADVERSE REACTIONS

In a total of 1836 patients in controlled and uncontrolled clinical trials, 14% of patients received amiodarone HCl injection for at least one week, 5% received it for at least 2 weeks, 2% received it for at least 3 weeks, and 1% received it for more than 3 weeks, without an increased incidence of severe adverse reactions. The mean duration of therapy in these studies was 5.6 days; median exposure was 3.7 days.

The most important treatment-emergent adverse effects were hypotension, asystole/cardiac arrest/ electromechanical dissociation (EMD), cardiogenic shock, congestive heart failure, bradycardia, liver function test abnormalities, VT, and AV block. Overall, treatment was discontinued for about 9% of the patients because of adverse effects. The most common adverse effects leading to discontinuation of amiodarone HCl injection therapy were hypotension (1.6%), asystole/cardiac arrest/EMD (1.2%), VT (1.1%), and cardiogenic shock (1%).

The following table lists the most common (incidence ≥ 2%) treatment-emergent adverse events during amiodarone HCl injection therapy considered at least possibly drug-related. These data were collected in clinical trials involving 1836 patients with life-threatening VT/VF. Data from all assigned treatment groups are pooled because none of the adverse events appeared to be dose-related.

SUMMARY TABULATION OF TREATMENT-EMERGENT

DRUG-RELATED STUDY EVENTS IN PATIENTS RECEIVING

AMIODARONE HCL INJECTION IN CONTROLLED AND OPEN-LABEL

STUDIES (≥ 2% INCIDENCE)

Other treatment-emergent possibly drug-related adverse events reported in less than 2% of patients receiving amiodarone HCl injection in controlled and uncontrolled studies included the following: abnormal kidney function, atrial fibrillation, diarrhea, increased ALT, increased AST, lung edema, nodal arrhythmia, prolonged QT interval, respiratory disorder, shock, sinus bradycardia, Stevens-Johnson syndrome, thrombocytopenia, VF, and vomiting.

Postmarketing Reports

In postmarketing surveillance, hypotension (sometimes fatal), sinus arrest, anaphylactic/anaphylactoid reaction (including shock), angioedema, hepatitis, cholestatic hepatitis, cirrhosis, pancreatitis, renal impairment, renal insufficiency, acute renal failure, bronchospasm, possibly fatal respiratory disorders (including distress, failure, arrest, and ARDS), bronchiolitis obliterans organizing pneumonia (possibly fatal), fever, dyspnea, cough, hemoptysis, wheezing, hypoxia, pulmonary infiltrates and/or mass, pleuritis, pseudotumor cerebri, syndrome of inappropriate antidiuretic hormone secretion (SIADH), thyroid nodules/thyroid cancer, toxic epidermal necrolysis (sometimes fatal), erythema multiforme, Stevens-Johnson syndrome, exfoliative dermatitis, skin cancer, vasculitis, pruritus, hemolytic anemia, aplastic anemia, pancytopenia, neutropenia, thrombocytopenia, agranulocytosis, granuloma, myopathy, muscle weakness, rhabdomyolysis, hallucination, confusional state, disorientation, delirium, epididymitis, and impotence also have been reported with amiodarone therapy.

Also, in patients receiving recommended dosages of amiodarone HCl injection, there have been postmarketing reports of the following injection site reactions: pain, erythema, edema, pigment changes, venous thrombosis, phlebitis, thrombophlebitis, cellulitis, necrosis, and skin sloughing (see DOSAGE & ADMINISTRATION).

OVERDOSAGE

There have been cases, some fatal, of amiodarone overdose. Effects of an inadvertent overdose of amiodarone HCl injection include hypotension, cardiogenic shock, bradycardia, AV block, and hepatotoxicity. Hypotension and cardiogenic shock should be treated by slowing the infusion rate or with standard therapy: vasopressor drugs, positive inotropic agents, and volume expansion. Bradycardia and AV block may require temporary pacing. Hepatic enzyme concentrations should be monitored closely. Amiodarone is not dialyzable.

DOSAGE & ADMINISTRATION

Amiodarone shows considerable interindividual variation in response. Thus, although a starting dose adequate to suppress life-threatening arrhythmias is needed, close monitoring with adjustment of dose as needed is essential. The recommended starting dose of amiodarone HCl injection is about 1000 mg over the first 24 hours of therapy, delivered by the following infusion regimen:

After the first 24 hours, the maintenance infusion rate of 0.5 mg/min (720 mg/24 hours) should be continued utilizing a concentration of 1 to 6 mg/mL (Amiodarone HCl Injection concentrations greater than 2 mg/mL should be administered via a central venous catheter). In the event of breakthrough episodes of VF or hemodynamically unstable VT, 150 mg supplemental infusions of amiodarone HCl injection mixed in 100 mL of D 5W may be administered. Such infusions should be administered over 10 minutes to minimize the potential for hypotension. The rate of the maintenance infusion may be increased to achieve effective arrhythmia suppression.

The first 24-hour dose may be individualized for each patient; however, in controlled clinical trials, mean daily doses above 2100 mg were associated with an increased risk of hypotension. The initial infusion rate should not exceed 30 mg/min.

Based on the experience from clinical studies of amiodarone HCl injection, a maintenance infusion of up to 0.5 mg/min can be cautiously continued for 2 to 3 weeks regardless of the patient's age, renal function, or left ventricular function. There has been limited experience in patients receiving amiodarone HCl injection for longer than 3 weeks.

The surface properties of solutions containing injectable amiodarone are altered such that the drop size may be reduced. This reduction may lead to underdosage of the patient by up to 30% if drop counter infusion sets are used. Amiodarone HCl injection must be delivered by a volumetric infusion pump.

Amiodarone HCl injection should, whenever possible, be administered through a central venous catheter dedicated to that purpose. An in-line filter should be used during administration.
Amiodarone HCl injection loading infusions at much higher concentrations and rates of infusion much faster than recommended have resulted in hepatocellular necrosis and acute renal failure, leading to death (see PRECAUTIONS, Liver Enzyme Elevations).

Amiodarone HCl injection concentrations greater than 3 mg/mL in D 5W have been associated with a high incidence of peripheral vein phlebitis; however, concentrations of 2.5 mg/mL or less appear to be less irritating. Therefore, for infusions longer than 1 hour, amiodarone HCl injection concentrations should not exceed 2 mg/mL unless a central venous catheter is used (see ADVERSE REACTIONS, Postmarketing Reports).

Amiodarone HCl injection infusions exceeding 2 hours must be administered in glass or polyolefin bottles containing D 5W. Use of evacuated glass containers for admixing amiodarone HCl injection is not recommended as incompatibility with a buffer in the container may cause precipitation.

It is well known that amiodarone adsorbs to polyvinyl chloride (PVC) tubing and the clinical trial dose administration schedule was designed to account for this adsorption. All of the clinical trials were conducted using PVC tubing and its use is therefore recommended. The concentrations and rates of infusion provided in DOSAGE & ADMINISTRATION reflect doses identified in these studies. Amiodarone HCl injection has been found to leach out plasticizers, including DEHP [di-(2-ethylhexyl)phthalate] from intravenous tubing (including PVC tubing). The degree of leaching increases when infusing amiodarone HCl injection at higher concentrations and lower flow rates than provided in DOSAGE & ADMINISTRATION. In addition, polysorbate 80, a component of amiodarone HCl injection, is also known to leach DEHP from PVC (see DESCRIPTION). Therefore, it is important that the recommendations in DOSAGE & ADMINISTRATION be followed closely.

Amiodarone HCl injection does not need to be protected from light during administration.

Note: Parenteral drug products should be inspected visually for particulate matter, whenever solution and container permit.

Admixture Incompatibility

Amiodarone HCl injection in D 5W is incompatible with the drugs shown below.

Intravenous to Oral Transition

Patients whose arrhythmias have been suppressed by amiodarone HCl injection may be switched to oral amiodarone. The optimal dose for changing from intravenous to oral administration of amiodarone will depend on the dose of amiodarone HCl injection already administered, as well as the bioavailability of oral amiodarone. When changing to oral amiodarone therapy, clinical monitoring is recommended, particularly for elderly patients.

Since there are some differences between the safety and efficacy profiles of the intravenous and oral formulations, the prescriber is advised to review the package insert for oral amiodarone when switching from intravenous to oral amiodarone therapy.

Since grapefruit juice is known to inhibit CYP3A4-mediated metabolism of oral amiodarone in the intestinal mucosa, resulting in increased plasma levels of amiodarone, grapefruit juice should not be taken during treatment with oral amiodarone (see PRECAUTIONS, Drug Interactions).

The following table provides suggested doses of oral amiodarone to be initiated after varying durations of amiodarone HCl injection administration. These recommendations are made on the basis of a comparable total body amount of amiodarone delivered by the intravenous and oral routes, based on 50% bioavailability of oral amiodarone.

HOW SUPPLIED

AMIODARONE HCI INJECTION is supplied in the following dosage forms.
NDC 51662-1363-1
AMIODARONE HCI INJECTION 150 mg/3 mL (50 mg/mL) 3 mL VIAL

HF Acquisition Co LLC, DBA HealthFirst
Mukilteo, WA 98275

Also supplied in the following manufacture supplied dosage forms

Amiodarone HCl Injection is supplied as:

Vial stoppers do not contain natural rubber latex.

Store at 20° to 25°C (68° to 77°F) [see USP Controlled Room Temperature].

Protect from light and excessive heat.

Use carton to protect contents from light until used.

SPL UNCLASSIFIED

45887H

Revised: April 2008